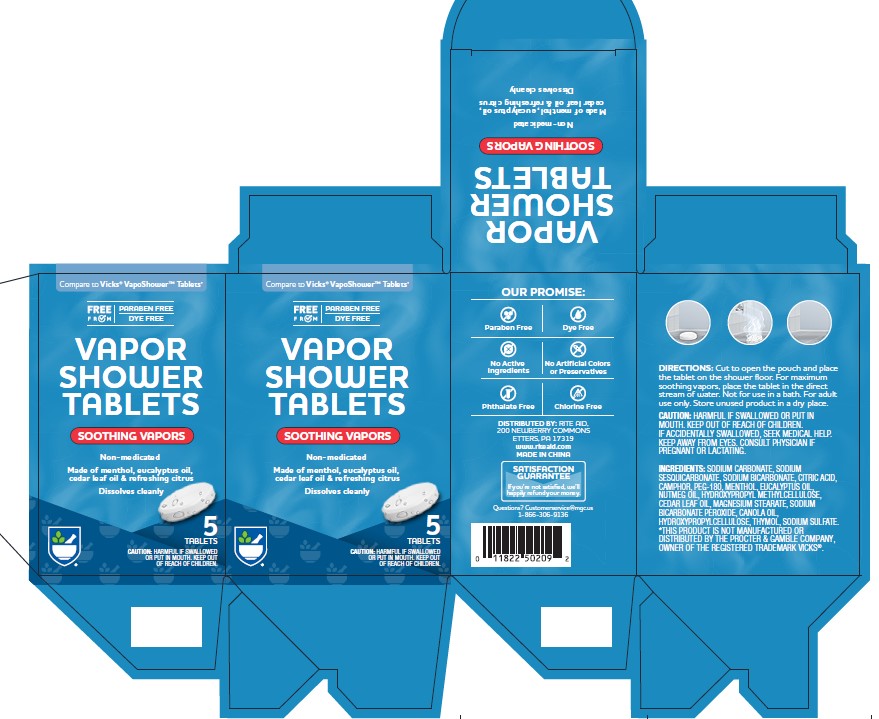 DRUG LABEL: Vapor Shower
NDC: 83698-003 | Form: TABLET
Manufacturer: Xiamen Kang Zhongyuan Biotechnology Co., Ltd.
Category: otc | Type: HUMAN OTC DRUG LABEL
Date: 20250130

ACTIVE INGREDIENTS: MENTHOL 0.45 mg/1 1
INACTIVE INGREDIENTS: SODIUM CARBONATE; SODIUM SESQUICARBONATE; SODIUM BICARBONATE; CITRIC ACID; CAMPHOR (SYNTHETIC); PEG-180; EUCALYPTUS GLOBULUS LEAF OIL; NUTMEG; HYDROXYPROPYL METHYLCELLULOSE; CEDAR LEAF OIL; MAGNESIUM STEARATE; SODIUM CARBONATE PEROXIDE; CANOLA OIL; HYDROXYPROPYLCELLULOSE; THYMOL

Shower tablet RA

Directions

Cut to open the pouch and place
the tablet on the shower floor. For maximum
soothing vapors, place the tablet in the direct
stream of water. Not for use in a bath. For adult
use only. Store unused product in a dry place.

WARNINGS

HARMFUL IF SWALLOWED OR PUT IN MOUTH.

KEEP OUT OF REACH OF CHILDREN.
IF ACCIDENTALLY SWALLOWED, SEEK MEDICAL HELP.
KEEP AWAY FROM EYES.

PREGNANCY OR BREAST FEEDING

CONSULT PHYSICIAN IF
PREGNANT OR LACTATING.

INACTIVE INGREDIENT

SODIUM CARBONATE, SODIUM
SESQUICARBONATE, SODIUM BICARBONATE, CITRIC ACID,
CAMPHOR, PEG-180, MENTHOL, EUCALYPTUS OIL,
NUTMEG OIL, HYDROXYPROPYL METHYLCELLULOSE,
CEDAR LEAF OIL, MAGNESIUM STEARATE, SODIUM
BICARBONATE PEROXIDE, CANOLA OIL,
HYDROXYPROPYLCELLULOSE, THYMOL, SODIUM SULFATE

PURPOSE

cough suppressant

ACTIVE INGREDIENT

Menthol

INDICATIONS AND USAGE

temporary relieves: ■ cough due to cold

PACKAGE LABEL

Add image transcription here...